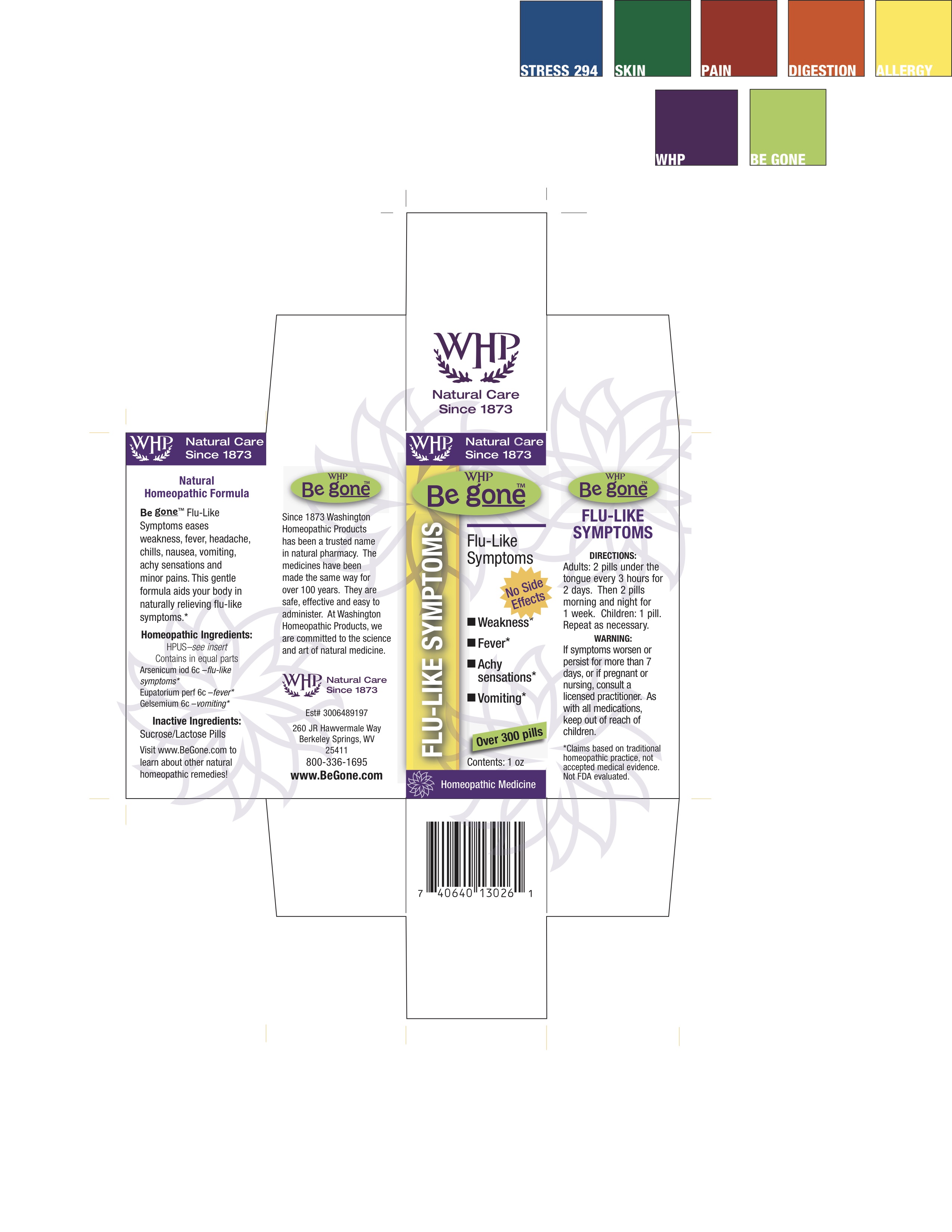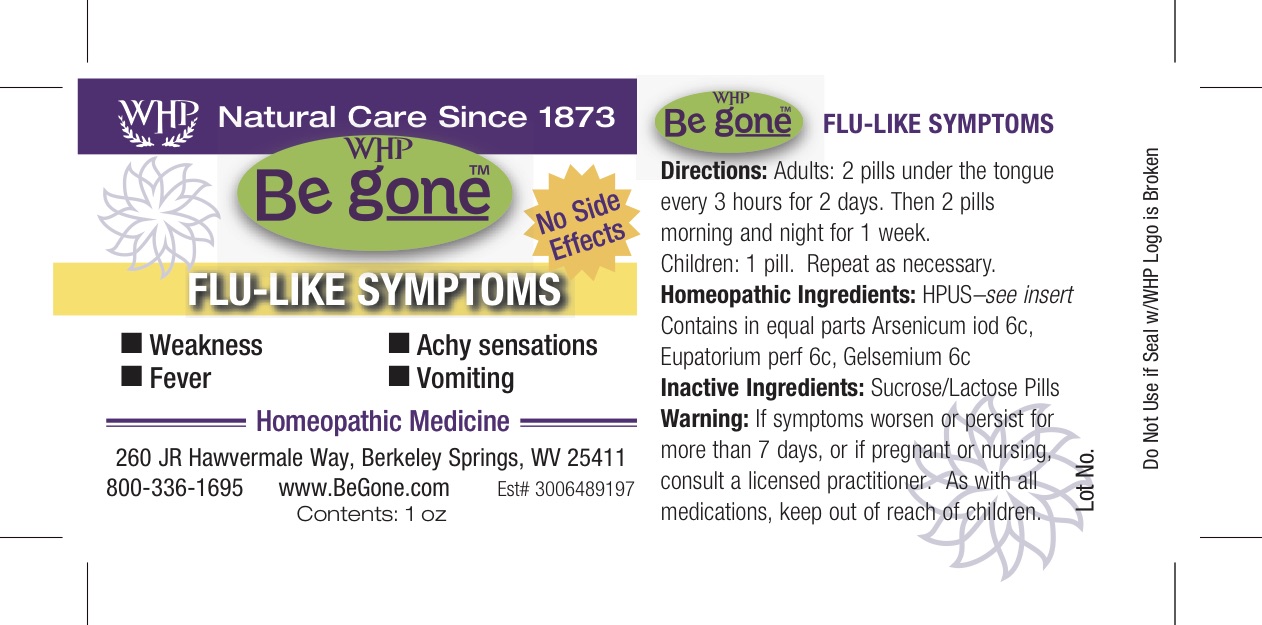 DRUG LABEL: WHP Be gone Flu-like Symptoms
NDC: 68428-734 | Form: PELLET
Manufacturer: Washington Homeopathic Products
Category: homeopathic | Type: HUMAN OTC DRUG LABEL
Date: 20181113

ACTIVE INGREDIENTS: ARSENIC TRIIODIDE 6 [hp_C]/28 g; EUPATORIUM PERFOLIATUM FLOWERING TOP 6 [hp_C]/28 g; GELSEMIUM SEMPERVIRENS ROOT 6 [hp_C]/28 g
INACTIVE INGREDIENTS: SUCROSE; LACTOSE

DRUG FACTS

ACTIVE INGREDIENTS

ARSENICUM IOD 6C

EUPATORIUM PERF 6C

GELSEMIUM 6C

USES

Eases weakness, fever, headache, chills, nausea, vomiting, achy sensations and minor pains.

KEEP OUT OF REACH OF CHILDREN

As with all medications, keep out of reach of children.

INDICATIONS

ARSENICUM IOD Flu-like symptoms

EUPATORIUM PERF Fever

GELSEMIUM Vomiting

STOP USE AND ASK DOCTOR

If symptoms persist/worsen or if pregnant/nursing, stop use and consult your practitioner.

*Claims based on traditional homeopathic practice, not accepted medical evidence. Not FDA evaluated.

DIRECTIONS

Adults 2 pellets every 3 hours for 2 days. Then 2 pellets morning and night for 2 weeks.

Children: 1 pellet. Repeat as necessary.

INACTIVE INGREDIENTS

Sucrose/Lactose

PRINCIPAL DISPLAY PANEL

WHP Be g oneTM Flu-like Symptoms label

WHP Be g oneTM Flu-like Symptoms box